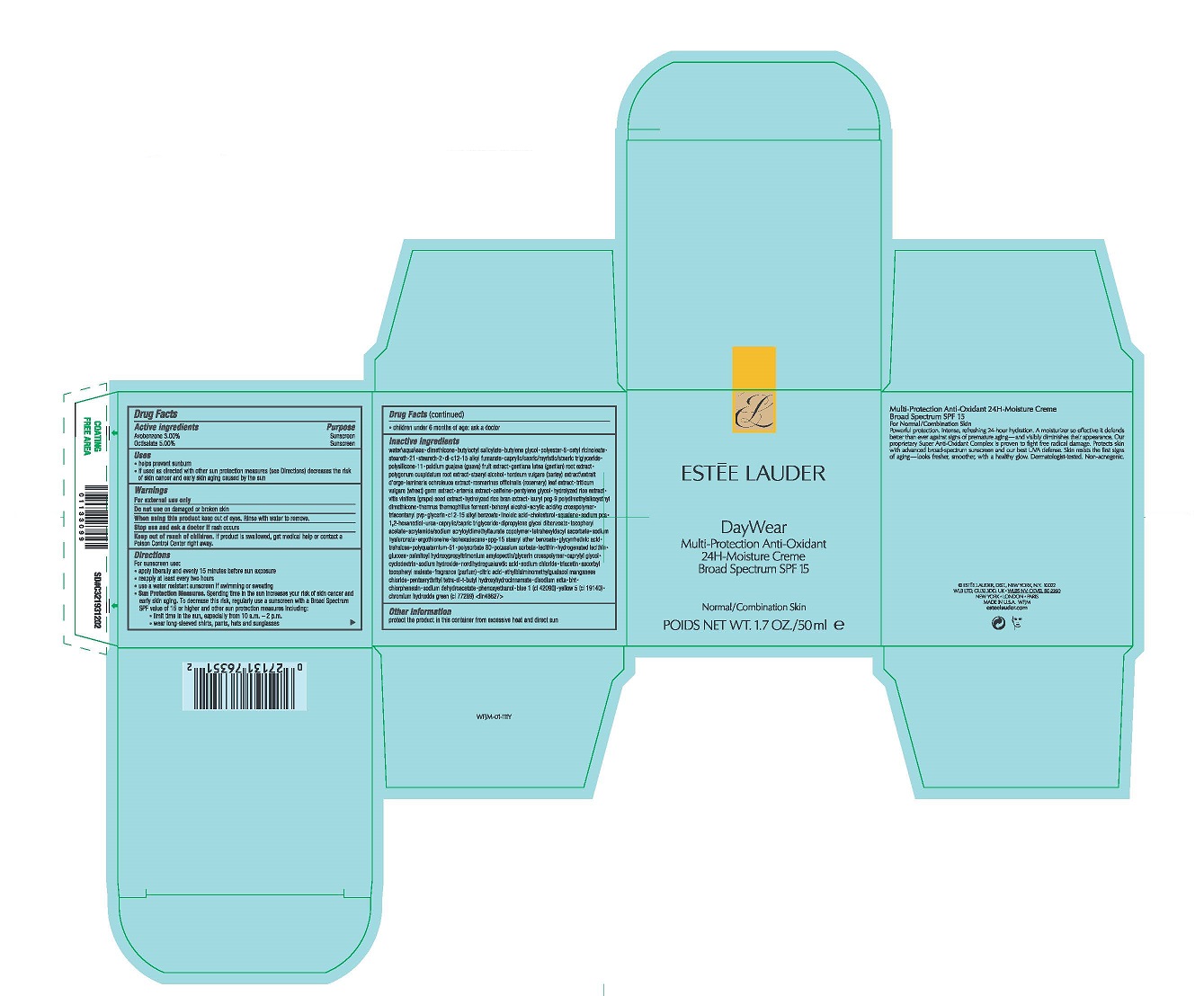 DRUG LABEL: DAYWEAR MULTI-PROTECTION ANTII-OXIDANT 24H-MOISTURE CREME BROAD SPECTRUM SPF 15  NORMAL/COMBINATION SKIN
NDC: 11559-049 | Form: CREAM
Manufacturer: ESTEE LAUDER INC
Category: otc | Type: HUMAN OTC DRUG LABEL
Date: 20250408

ACTIVE INGREDIENTS: AVOBENZONE 30 mg/1 mL; OCTISALATE 50 mg/1 mL
INACTIVE INGREDIENTS: ROSEMARY; WHEAT GERM; FUMARIA OFFICINALIS FLOWERING TOP; CAFFEINE; PENTYLENE GLYCOL; RICE GERM; VITIS VINIFERA SEED; LAURYL PEG-9 POLYDIMETHYLSILOXYETHYL DIMETHICONE; THERMUS THERMOPHILUS LYSATE; DOCOSANOL; TRICONTANYL POVIDONE; GLYCERIN; ALKYL (C12-15) BENZOATE; LINOLEIC ACID; CHOLESTEROL; SQUALANE; SODIUM PYRROLIDONE CARBOXYLATE; 1,2-HEXANEDIOL; UREA; MEDIUM-CHAIN TRIGLYCERIDES; DIPROPYLENE GLYCOL DIBENZOATE; .ALPHA.-TOCOPHEROL ACETATE; TETRAHEXYLDECYL ASCORBATE; HYALURONATE SODIUM; ERGOTHIONEINE; ISOHEXADECANE; PPG-15 STEARYL ETHER BENZOATE; ENOXOLONE; TREHALOSE; POLYSORBATE 80; HYDROGENATED SOYBEAN LECITHIN; CAPRYLYL GLYCOL; SODIUM HYDROXIDE; SODIUM CHLORIDE; ASCORBYL TOCOPHERYL MALEATE; CITRIC ACID MONOHYDRATE; ETHYLBISIMINOMETHYLGUAIACOL MANGANESE CHLORIDE; PENTAERYTHRITOL TETRAKIS(3-(3,5-DI-TERT-BUTYL-4-HYDROXYPHENYL)PROPIONATE); EDETATE DISODIUM ANHYDROUS; BUTYLATED HYDROXYTOLUENE; SODIUM DEHYDROACETATE; PHENOXYETHANOL; FD&C BLUE NO. 1; FD&C YELLOW NO. 5; CHROMIUM HYDROXIDE GREEN; CHLORPHENESIN; TRIACETIN; NORDIHYDROGUAIARETIC ACID, (+/-)-; .BETA.-CYCLODEXTRIN SULFOBUTYL ETHER; TRIMETHYLPENTANEDIOL/ADIPIC ACID/GLYCERIN CROSSPOLYMER (25000 MPA.S); GLUCOSE 1,6-BISPHOSPHATE; LECITHIN, SOYBEAN; POTASSIUM SORBATE; POLYQUATERNIUM-51 (2-METHACRYLOYLOXYETHYL PHOSPHORYLCHOLINE/N-BUTYL METHACRYLATE; 3:7); ACRYLAMIDE; ACRYLIC ACID; RICE BRAN; WATER; DIMETHICONE; BUTYLOCTYL SALICYLATE; BUTYLENE GLYCOL; POLYESTER-8 (1400 MW, CYANODIPHENYLPROPENOYL CAPPED); CETYL RICINOLEATE; STEARETH-21; STEARETH-2; DI-C12-15 ALKYL FUMARATE; CAPRYLIC/CAPRIC/PALMITIC/STEARIC TRIGLYCERIDE; GUAVA; GENTIANA LUTEA ROOT; REYNOUTRIA JAPONICA ROOT; STEARYL ALCOHOL; BARLEY; LAMINARIA OCHROLEUCA

DAYWEAR MULTI-PROTECTION ANTI-OXIDANT 24H-MOISTURE CREME BROAD SPECTRUM SPF 15 NORMAL/COMBINATION SKIN

Drug Facts

ACTIVE INGREDIENT

Active ingredients | Purpose
Avobenzone 3.00% | Sunscreen
Octisalate 5.00% | Sunscreen

Uses

- helps prevent sunburn
- if used as directed with other sun protection measures (see Directions) decreases the risk of skin cancer and early skin aging caused by the sun

Warnings

For external use only

Do not use on damaged or broken skin

When using this product keep out of eyes. Rinse with water to remove.

Stop use and ask a doctor if rash occurs

Keep out of reach of children. If product is swallowed, get medical help or contact a Poison Control Center right away.

Directions

For sunscreen use:

- apply liberally and evenly 15 minutes before sun exposure
- reapply at least every two hours
- use a water resistant sunscreen if swimming or sweating
- Sun Protection Measures. Spending time in the sun increases your risk of skin cancer and early skin aging. To decrease this risk, regularly use a sunscreen with a Broad Spectrum SPF value of 15 or higher and other sun protection measures including:
  - limit time in the sun, especially from 10 a.m. – 2 p.m.
  - wear long-sleeved shirts, pants, hats and sunglasses
- children under 6 months of age: ask a doctor

Inactive ingredients

water\aqua\eau • dimethicone • butyloctyl salicylate • butylene glycol • polyester-8 • cetyl ricinoleate • steareth-21 • steareth-2 • di-c12-15 alkyl fumarate • caprylic/capric/myristic/stearic triglyceride • polysilicone-11 • psidium guajava (guava) fruit extract • gentiana lutea (gentian) root extract • polygonum cuspidatum root extract • stearyl alcohol • hordeum vulgare (barley) extract\extrait d'orge • laminaria ochroleuca extract • rosmarinus officinalis (rosemary) leaf extract • triticum vulgare (wheat) germ extract • artemia extract • caffeine • pentylene glycol • hydrolyzed rice extract • vitis vinifera (grape) seed extract • hydrolyzed rice bran extract • lauryl peg-9 polydimethylsiloxyethyl dimethicone • thermus thermophillus ferment • behenyl alcohol • acrylic acid/vp crosspolymer • triacontanyl pvp • glycerin • c12-15 alkyl benzoate • linoleic acid • cholesterol • squalane • sodium pca • 1,2-hexanediol • urea • caprylic/capric triglyceride • dipropylene glycol dibenzoate • tocopheryl acetate • acrylamide/sodium acryloyldimethyltaurate copolymer • tetrahexyldecyl ascorbate • sodium hyaluronate • ergothioneine • isohexadecane • ppg-15 stearyl ether benzoate • glycyrrhetinic acid • trehalose • polyquaternium-51 • polysorbate 80 • potassium sorbate • lecithin • hydrogenated lecithin • glucose • palmitoyl hydroxypropyltrimonium amylopectin/glycerin crosspolymer • caprylyl glycol • cyclodextrin • sodium hydroxide • nordihydroguaiaretic acid • sodium chloride • triacetin • ascorbyl tocopheryl maleate • fragrance (parfum) • citric acid • ethylbisiminomethylguaiacol manganese chloride • pentaerythrityl tetra-di-t-butyl hydroxyhydrocinnamate • disodium edta • bht • chlorphenesin • sodium dehydroacetate • phenoxyethanol • blue 1 (ci 42090) • yellow 5 (ci 19140) • chromium hydroxide green (ci 77289) <iln48627>

Other information

protect the product in this container from excessive heat and direct sun

PRINCIPAL DISPLAY PANEL - 50 ml Jar Carton

ESTĒE LAUDER

DayWear
Multi-Protection
Anti-Oxidant
24H-Moisture Creme
Broad Spectrum SPF 15

NORMAL/COMBINATION SKIN

POIDS NET WT. 1.7 OZ. / 50 ml e